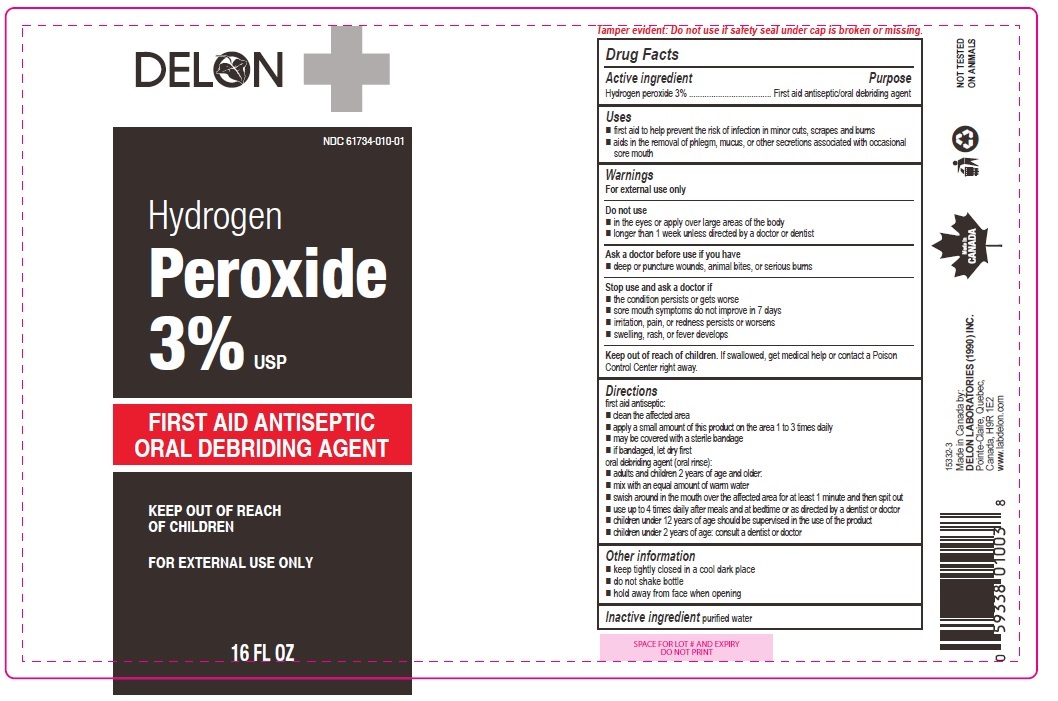 DRUG LABEL: Hydrogen Peroxide
NDC: 61734-010 | Form: SOLUTION
Manufacturer: Delon Laboratories (1990) Ltd
Category: otc | Type: HUMAN OTC DRUG LABEL
Date: 20251016

ACTIVE INGREDIENTS: HYDROGEN PEROXIDE 3 mL/100 mL
INACTIVE INGREDIENTS: WATER

Hydrogen Peroxide 3%

Active ingredient

Hydrogen peroxide 3%

Purpose

first aid antiseptic / oral debriding agent

Uses

- first aid to help prevent the risk of infection in minor cuts, scrapes and burns
- aids in the removal of phlegm, mucus, or other secretions associated with occasional sore mouth

Warnings

For external use only

Do not use

- in the eyes or apply over large areas of the body
- longer than 1 week unless directed by a doctor or dentist

Ask a doctor before use if you have

- deep or puncture wounds, animal bites, or serious burns

Stop use and ask a doctor if

- the condition persists or gets worse
- sore mouth symptoms do not improve in 7 days
- irritation, pain, or redness persists or worsens
- swelling, rash, or fever develops

Keep out of reach of children. If swallowed, get medical help or contact a Poison Control Center right away.

Directions

first aid antiseptic:

- clean the affected area
- apply a small amount of this product on the area 1 to 3 times daily
- may be covered with a sterile bandage
- if bandaged, let dry first

oral debriding agent (oral rinse):

- adults and children 2 years of age and older:
- mix with an equal amount of warm water
- swish around in the mouth over the affected area for at least 1 minute and then spit out
- use up to 4 times daily after meals and at bedtime or as directed by a dentist or doctor

- children under 12 years of age should be supervised in the use of the product
- children under 2 years of age: consult a dentist or doctor

Other information

- keep tightly closed in a cool dark place
- do not shake bottle
- hold away from face when opening

Inactive ingredient

purified water